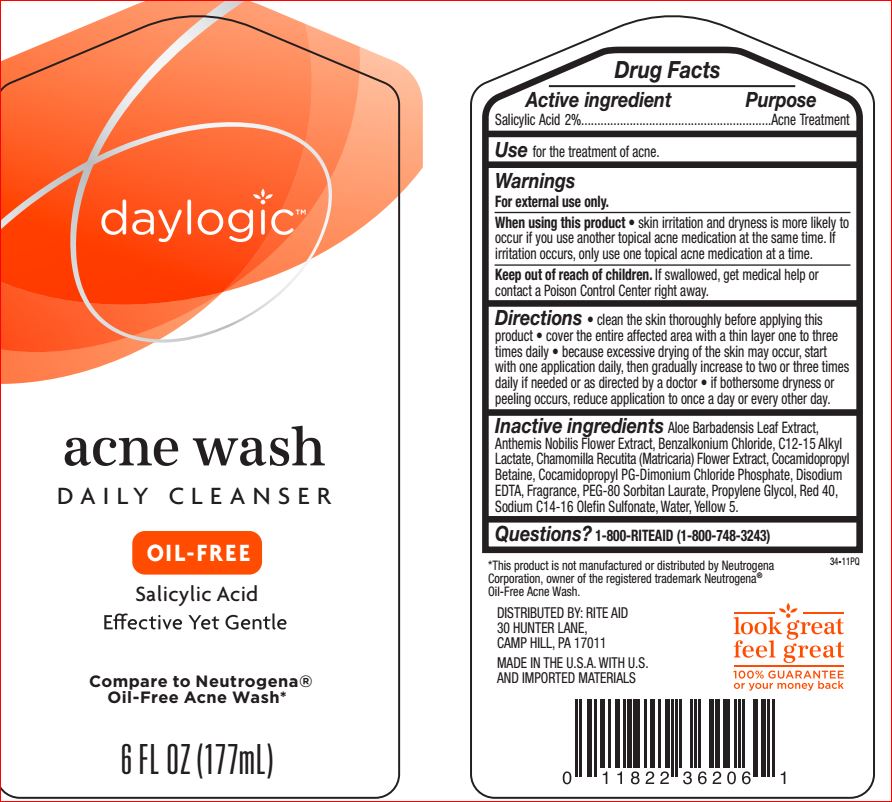 DRUG LABEL: Acne Wash Daily Cleanser
NDC: 11822-7779 | Form: LIQUID
Manufacturer: Rite Aid
Category: otc | Type: HUMAN OTC DRUG LABEL
Date: 20180327

ACTIVE INGREDIENTS: Salicylic Acid 2 g/100 mL
INACTIVE INGREDIENTS: Water; Sodium C14-16 Olefin Sulfonate; Cocamidopropyl Betaine; CHAMOMILE; Cocamidopropyl PG-Dimonium Chloride Phosphate; Propylene Glycol; ALOE; CHAMAEMELUM NOBILE FLOWER; C12-15 Alkyl Lactate; PEG-80 Sorbitan Laurate; EDETATE DISODIUM; Benzalkonium Chloride; FD&C YELLOW NO. 5; FD&C RED NO. 40

Drug Facts

Active ingredient Purpose
Salicylic Acid 2%......................................................................Acne Treatment

Use

for the treatment of acne

Warnings For external use only.

Allergy alert: Do not use this product if you have a known allergy to salicylic acid
When using this product • skin irritation and dryness is more likely to occur
if you use another topical acne medication at the same time. If irritation
occurs, only use one topical acne medication at a time. • Avoid contact with
eyes. If contact occurs, flush thoroughly with water.

Keep out of reach of children.

If swallowed, get medical help or contact a
Poison Control Center right away

Directions

Cleanse twice a day. • Wet face. • Apply to hands, add
water and work into lather. • Massage face gently, rinse thoroughly.

Inactive ingredients

Aloe Barbadensis Leaf Extract
Anthemis Nobilis Flower Extract
Benzalkonium Chloride
C12-15 Alkyl Lactate
Chamomilla Recutita (Matricaria) Flower Extract
Cocamidopropyl Betaine
Cocamidopropyl PG-Dimonium Chloride Phosphate
Disodium EDTA
Fragrance
PEG-80 Sorbitan Laurate
Propylene Glycol
Red 40
Sodium C14-16 Olefin Sulfonate
Water
Yellow 5